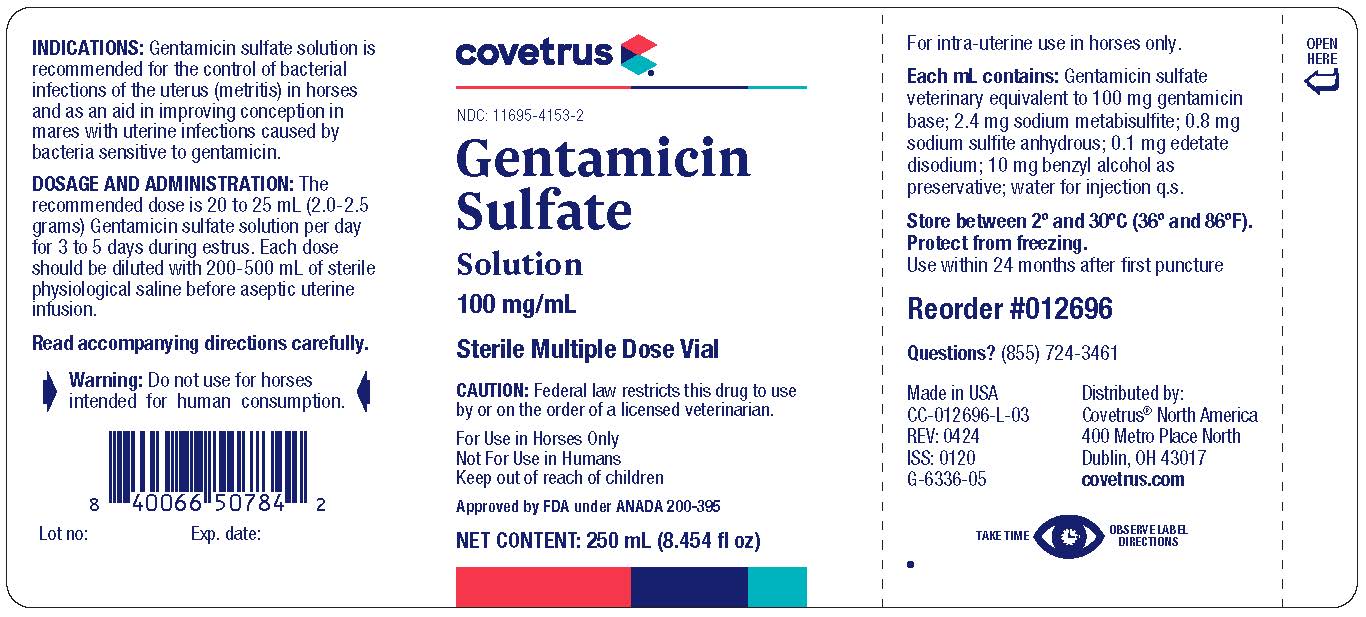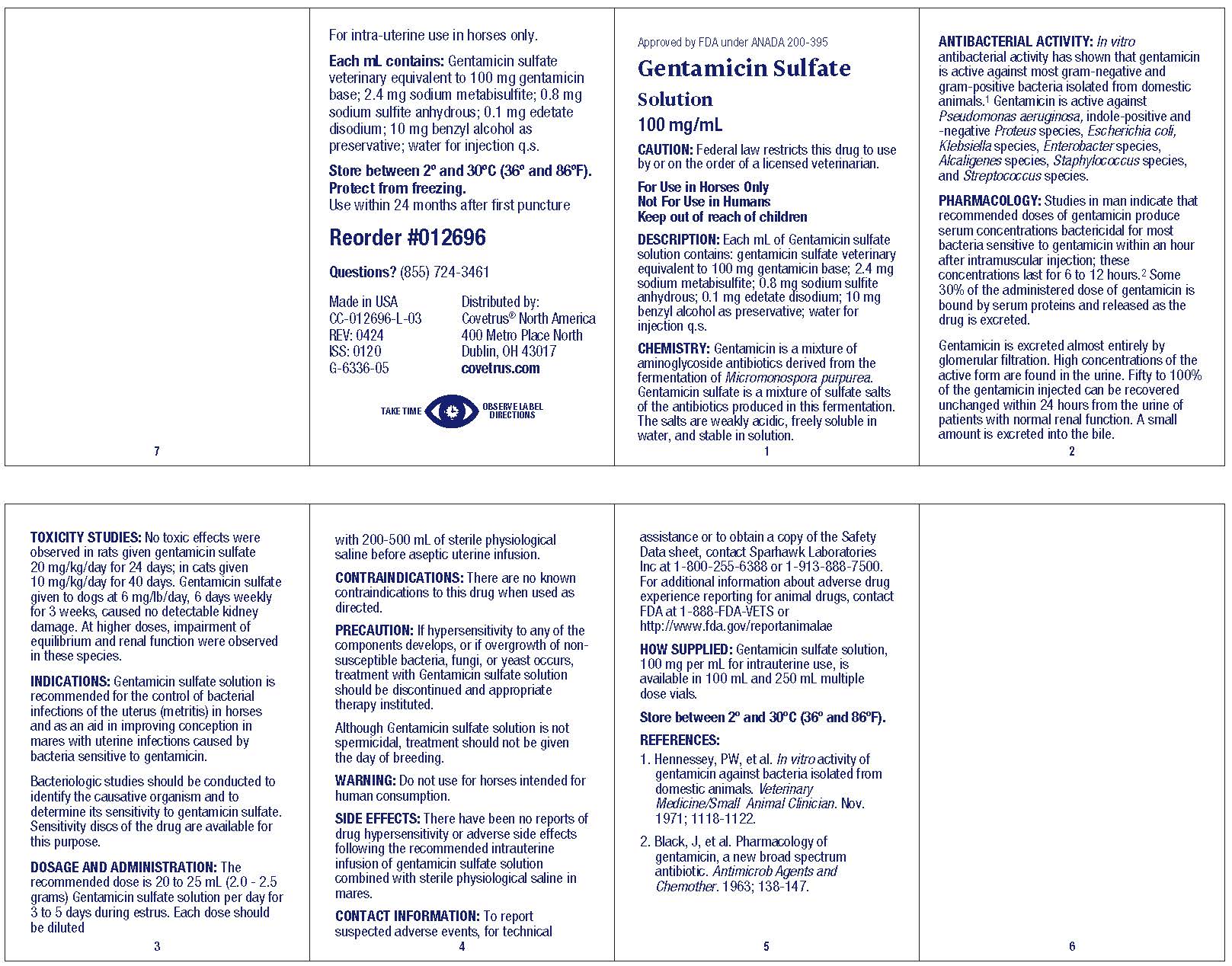 DRUG LABEL: GENTAMICIN SULFATE
NDC: 11695-4153 | Form: SOLUTION
Manufacturer: Covetrus North America
Category: animal | Type: PRESCRIPTION ANIMAL DRUG LABEL
Date: 20250429

ACTIVE INGREDIENTS: GENTAMICIN SULFATE 100 mg/1 mL
INACTIVE INGREDIENTS: BENZYL ALCOHOL; EDETATE DISODIUM; SODIUM METABISULFITE; SODIUM SULFITE; Water

GENTAMICIN Sulfate Solution

GENERAL PRECAUTIONS

Approved by FDA under ANADA 200-395
Gentamicin Sulfate
Solution
100 mg/mL
CAUTION: Federal law restricts this drug to use
by or on the order of a licensed veterinarian.
For Use in Horses Only
Not For Use in Humans
Keep out of reach of children

DESCRIPTION

Each mL of Gentamicin Sulfate Solution contains gentamicin sulfate solution veterinary equivalent to 100 mg gentamicin base; 2.4 mg sodium metabisulfite; 0.8 mg sodium sulfite, anhydrous; 0.1 mg edetate disodium; 10 mg benzyl alcohol as preservative; water for injection q.s.

CLINICAL STUDIES

CHEMISTRY: Gentamicin is a mixture of aminglycoside antibiotics derived from the fermentation of Micromonospora purpurea. Gentamicin sulfate is a mixture of sulfate salts of the antibiotics produced in this fermentation. The salts are weakly acidic, freely soluble in water, and stable in solution.

ANTIBACTERIAL ACTIVITY: In Vitro antibacterial activity has shown that gentamicin is active against most gram-negative and gram-positive bacteria isolated from domestic animals.^1 Gentamicin is active against Pseudomonas aeruginosa, indole-positive and -negative Proteus species, Escherichia coli, Klebsiella species, Enterobacter species, Alcaligenes species, Staphylococcus species, and Streptococcus species.

PHARMACOLOGY: Studies in man indicate that recommended doses of gentamicin produce serum concentrations bactericidal for most bacteria sensitive to gentamicin within an hour after intramuscular injection; these concentrations last for 6 to 12 hours.^2 Some 30% of the administered dose of gentamicin is bound by serum proteins and released as the drug is excreted.

Gentamicin is excreted almost entirely by glomerular filtration. High concentrations of the active form are found in the urine. Fifty to 100% of the gentamicin injected can be recovered unchanged within 24 hours from the urine of patients with normal renal function. A small amount is excreted into the bile.

TOXICITY STUDIES: No toxic effects were observed in rats given gentamicin sulfate 20 mg/kg/day for 24 days; in cats given 10 mg/kg/day for 40 days. Gentamicin sulfate given to dogs at 6 mg/lb/day, 6 days weekly for 3 weeks, caused no detectable kidney damage. At higher doses, impairment of equilibrium and renal function were observed in these species.

INDICATIONS

Gentamicin sulfate solution is recommended for the control of bacterial infections of the uterus (metritis) in horses and as an aid in improving conception in mares with uterine infections caused by bacteria sensitive to gentamicin.

Bacteriologic studies should be conducted to identify the causative organism and to determine its sensitivity to gentamicin sulfate. Sensitivity discs of the drug are available for this purpose.

DOSAGE AND ADMINISTRATION

The recommended dose is 20 to 25 mL (2.0 - 2.5 grams) gentamicin sulfate solution per day for 3 to 5 days during estrus. Each dose should be diluted with 200-500 mL of sterile physiological saline before aseptic uterine infusion.

CONTRAINDICATIONS

There are no known contraindications to this drug when used as directed.

PRECAUTION

If hypersensitivity to any of the components develops, or if overgrowth of nonsusceptible bacteria, fungi, or yeasts occurs, treatment with Gentamicin Sulfate Solution should be discontinued and appropriate therapy instituted.

Although Gentamicin Sulfate Solution is not spermicidal, treatment should not be given the day of breeding.

Warning: Do not use for horses intended for human consumption.

SIDE EFFECTS

There have been no reports of drug hypersensitivity or adverse side effects following the recommended intrauterine infusion of gentamicin sulfate solution combined with sterile physiological saline in mares.

CONTACT INFORMATION

To report suspected adverse events, for technical assistance or to obtain a copy of the Safety Data sheet, contact Sparhawk Laboratories Inc at 1-800-255-6388 or 1-913-888-7500. For additional information about adverse drug experience reporting for animal drugs, contact FDA at 1-888-FDA-VETS or http://www.fda.gov/reportanimalae

HOW SUPPLIED

Gentamicin Sulfate Solution, 100 mg per mL for intrauterine use, is available in 100 mL and 250 mL multiple dose vials.

STORAGE AND HANDLING

Store between 2oand 30oC (36o and 86oF).

REFERENCES

1. Hennessey, PW, et al.In vitro activity of gentamicin against bacteria isolated from domestic animals.Veterinary Medicine/Small Animal Clinician, Nov. 1971; 1118-1122.

2. Black, J, et al. Pharmacology of gentamicin, a new broad spectrum antibiotic.Antimicrob Agents and Chemother. 1963, 138-147.

DESCRIPTION

For intra-uterine use in horses only.

Each mL contains: Gentamicin sulfate veterinary equivalent to 100 mg gentamicin base; 2.4 mg sodium metabisulfite; 0.8 mg sodium sulfite, anhydrous; 0.1 mg edetate disodium; 10 mg benzyl alcohol as preservative; water for injection q.s.
Store between 2o and 30oC (36o and 86oF).
Protect from freezing.

TAKE TIME OBSERVE LABEL DIRECTIONS